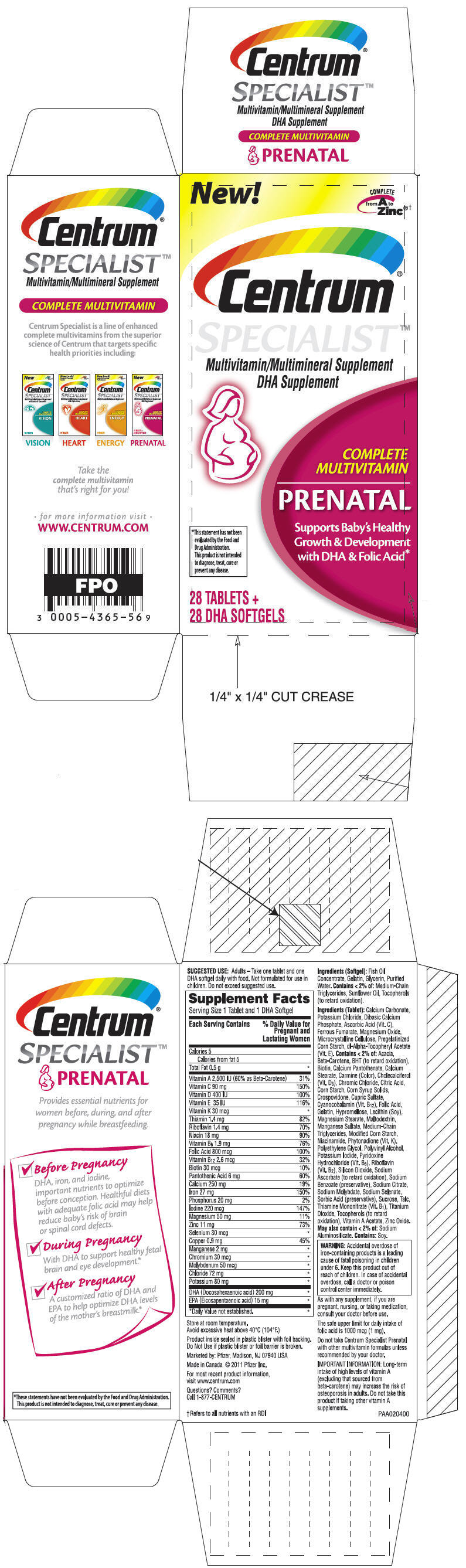 DRUG LABEL: Centrum Specialist Prenatal
NDC: 0005-4365 | Form: KIT | Route: ORAL
Manufacturer: Wyeth Pharmaceutical Division of Wyeth Holdings LLC
Category: other | Type: DIETARY SUPPLEMENT
Date: 20191209

ACTIVE INGREDIENTS: VITAMIN A ACETATE 1000 [iU]/1 1; BETA CAROTENE 1500 [iU]/1 1; ASCORBIC ACID 90 mg/1 1; CHOLECALCIFEROL 400 [iU]/1 1; .ALPHA.-TOCOPHEROL ACETATE 35 [iU]/1 1; PHYTONADIONE 30 ug/1 1; THIAMINE MONONITRATE 1.4 mg/1 1; RIBOFLAVIN 1.4 mg/1 1; NIACINAMIDE 18 mg/1 1; PYRIDOXINE HYDROCHLORIDE 1.9 mg/1 1; FOLIC ACID 800 ug/1 1; CYANOCOBALAMIN 2.6 mg/1 1; BIOTIN 30 ug/1 1; CALCIUM PANTOTHENATE 6 mg/1 1; ANHYDROUS DIBASIC CALCIUM PHOSPHATE 250 mg/1 1; FERROUS FUMARATE 27 mg/1 1; POTASSIUM IODIDE 220 ug/1 1; MAGNESIUM 50 mg/1 1; ZINC OXIDE 11 mg/1 1; SODIUM SELENATE 30 ug/1 1; CUPRIC SULFATE 0.9 mg/1 1; CHROMIC CHLORIDE 30 ug/1 1; MANGANESE SULFATE ANHYDROUS 2 mg/1 1; SODIUM MOLYBDATE 50 ug/1 1; CHLORIDE ION 72 mg/1 1; POTASSIUM CHLORIDE 80 mg/1 1; DOCONEXENT 200 mg/1 1; ICOSAPENT 15 mg/1 1
INACTIVE INGREDIENTS: MICROCRYSTALLINE CELLULOSE; MALTODEXTRIN; PIGMENT RED 5; GELATIN, UNSPECIFIED; CROSPOVIDONE (15 MPA.S AT 5%); LECITHIN, SOYBEAN; POLYETHYLENE GLYCOL, UNSPECIFIED; POLYVINYL ALCOHOL, UNSPECIFIED; SILICON DIOXIDE; STEARIC ACID; TALC; TITANIUM DIOXIDE; TOCOPHEROL; GELATIN, UNSPECIFIED; GLYCERIN; MEDIUM-CHAIN TRIGLYCERIDES; WATER; SUNFLOWER OIL; TOCOPHEROL

Centrum®
SPECIALIST™
PRENATAL

SUGGESTED USE

Adults

Take one tablet and one DHA softgel daily with food. Not formulated for use in children. Do not exceed suggested use.

STATEMENT OF IDENTITY

Supplement Facts
Serving Size 1 Tablet and 1 DHA Softgel
Each Serving Contains | % Daily Value for Pregnant and Lactating Women
Calories 5
Calories from fat 5
Total Fat 0.5 g | [Daily Value not established.]
Vitamin A 2,500 IU (60% as Beta-Carotene) | 31%
Vitamin C 90 mg | 150%
Vitamin D 400 IU | 100%
Vitamin E 35 IU | 116%
Vitamin K 30 mcg
Thiamin 1.4 mg | 82%
Riboflavin 1.4 mg | 70%
Niacin 18 mg | 90%
Vitamin B6 1.9 mg | 76%
Folic Acid 800 mcg | 100%
Vitamin B12 2.6 mcg | 32%
Biotin 30 mcg | 10%
Pantothenic Acid 6 mg | 60%
Calcium 250 mg | 19%
Iron 27 mg | 150%
Phosphorus 20 mg | 2%
Iodine 220 mcg | 147%
Magnesium 50 mg | 11%
Zinc 11 mg | 73%
Selenium 30 mcg
Copper 0.9 mg | 45%
Manganese 2 mg
Chromium 30 mcg
Molybdenum 50 mcg
Chloride 72 mg
Potassium 80 mg
DHA (Docosahexaenoic acid) 200 mg
EPA (Eicosapentaenoic acid) 15 mg

SAFE HANDLING WARNING

Store at room temperature.
Avoid excessive heat above 40°C (104°F.)

Product inside sealed in plastic blister with foil backing.
Do Not Use if plastic blister or foil barrier is broken.

HEALTH CLAIM

Marketed by: Pfizer, Madison, NJ 07940 USA

Made in Canada © 2011 Pfizer Inc.

For most recent product information, visit www.centrum.com

Questions? Comments?

Call 1-877-CENTRUM

Ingredients (Softgel)

Fish Oil Concentrate, Gelatin, Glycerin, Purified Water. Contains < 2% of: Medium-Chain Triglycerides, Sunflower Oil, Tocopherols (to retard oxidation).

Ingredients (Tablet)

Calcium Carbonate, Potassium Chloride, Dibasic Calcium Phosphate, Ascorbic Acid (Vit. C), Ferrous Fumarate, Magnesium Oxide, Microcrystalline Cellulose, Pregelatinized Corn Starch, dl-Alpha-Tocopheryl Acetate (Vit. E). Contains < 2% of: Acacia, Beta-Carotene, BHT (to retard oxidation), Biotin, Calcium Pantothenate, Calcium Stearate, Carmine (Color), Cholecalciferol (Vit. D3), Chromic Chloride, Citric Acid, Corn Starch, Corn Syrup Solids, Crospovidone, Cupric Sulfate, Cyanocobalamin (Vit. B12), Folic Acid, Gelatin, Hypromellose, Lecithin (Soy), Magnesium Stearate, Maltodextrin, Manganese Sulfate, Medium-Chain Triglycerides, Modified Corn Starch, Niacinamide, Phytonadione (Vit. K), Polyethylene Glycol, Polyvinyl Alcohol, Potassium Iodide, Pyridoxine Hydrochloride (Vit. B6), Riboflavin (Vit. B2), Silicon Dioxide, Sodium Ascorbate (to retard oxidation), Sodium Benzoate (preservative), Sodium Citrate, Sodium Molybdate, Sodium Selenate, Sorbic Acid (preservative), Sucrose, Talc, Thiamine Mononitrate, (Vit. B1), Titanium Dioxide, Tocopherols (to retard oxidation), Vitamin A Acetate, Zinc Oxide.

STATEMENT OF IDENTITY

May also contain < 2% of: Sodium Aluminosilicate. Contains: Soy.

WARNINGS

WARNING: Accidental overdose of iron-containing products is a leading cause of fatal poisoning in children under 6. Keep this product out of reach of children. In case of accidental overdose, call a doctor or poison control center immediately.

DOSAGE AND ADMINISTRATION

As with any supplement, if you are pregnant, nursing, or taking medication, consult your doctor before use.

The safe upper limit for daily intake of folic acid is 1000 mcg (1 mg).

Do not take Centrum Specialist Prenatal with other multivitamin formulas unless recommended by your doctor.

IMPORTANT INFORMATION

Long-term intake of high levels of vitamin A (excluding that sourced from beta-carotene) may increase the risk of osteoporosis in adults. Do not take this product if taking other vitamin A supplements.

HEALTH CLAIM

PAA020400

PRINCIPAL DISPLAY PANEL - Kit Carton

New!

COMPLETE
from A to
Zinc®†

Centrum®
SPECIALIST™

Multivitamin/Multimineral Supplement
DHA Supplement

COMPLETE
MULTIVITAMIN

PRENATAL

Supports Baby's Healthy
Growth & Development
with DHA & Folic Acid*

*This statement has not been
evaluated by the Food and
Drug Administration.
This product is not intended
to diagnose, treat, cure or
prevent any disease.

28 TABLETS +
28 DHA SOFTGELS